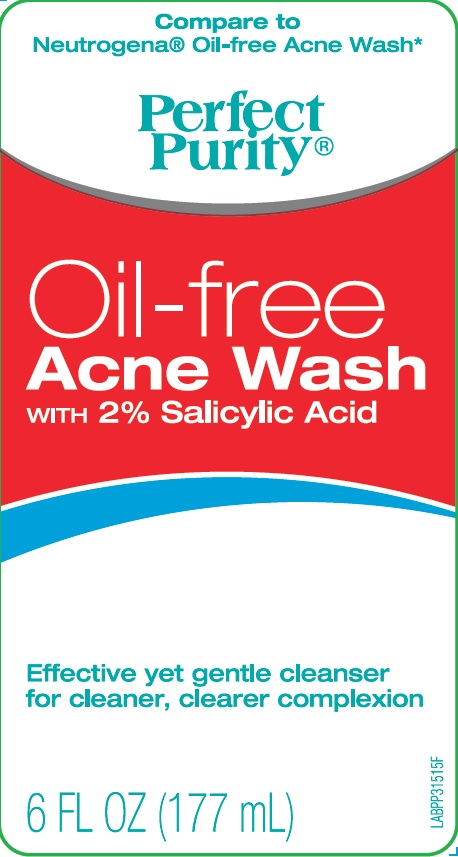 DRUG LABEL: Perfect Purity Oil Free Acne Wash
NDC: 71319-009 | Form: RINSE
Manufacturer: 9338-9641 Quebec Inc
Category: otc | Type: HUMAN OTC DRUG LABEL
Date: 20170313

ACTIVE INGREDIENTS: SALICYLIC ACID 2 g/100 g
INACTIVE INGREDIENTS: WATER; SODIUM LAURETH-3 SULFATE; COCAMIDOPROPYL BETAINE; PEG-150 DISTEARATE; PROPYLENE GLYCOL; COCO MONOETHANOLAMIDE; PEG-80 SORBITAN LAURATE; DIPROPYLENE GLYCOL; SODIUM CHLORIDE; METHYLISOTHIAZOLINONE; METHYLCHLOROISOTHIAZOLINONE; ALOE VERA LEAF; CHAMAEMELUM NOBILE FLOWER; EDETATE DISODIUM ANHYDROUS; FD&C YELLOW NO. 5; FD&C RED NO. 40

Active Ingredient

Salicylic Acid 2%

Purpose

Acne Treatment Wash

Use

- for the treatment of acne

Warnings

For external use only.

Ask a doctor or pharmacist before use if

you are using other topical acne medication at the same time or immediately following use of this product. This may increase dryness or irritation of the skin. If this occurs, only one medication should be used, unless directed by a doctor.

When using this product

do not use in or near the eyes. In case of contact, rinse eyes thoroughly with water.

Keep out of reach of children

If swallowed, get medical help or contact a Poison Control Center right away

Directions

- use twice daily
- apply water to face and hands
- dispense into hands and lather
- apply to face, nose area and neck
- gently massage into skin
- rinse thoroughly with tepid water.

INACTIVE INGREDIENT

Water, Sodium Laureth Sulfate, Cocamidopropyl Betaine, PEG-150 Distearate, Propylene Glycol, Cocamide MEA, PEG-80 Sorbitan Laurate, Dipropylene Glycol, Sodium Chloride, Fragrance, Methylisothiazolinone, Methylchloroisothiazolinone, Aloe Barbadensis Leaf Extract, Anthemis Nobilis Flower Extract, Disodium EDTA, Yellow 5 (19140), Red 40 (Cl 1605)

Questions

1-866-379-4222 or visit www.davioninc.com

Principal Display Panel

NDC 71319-009-06

Compare to Neutrogena Oil-free Acne Wash

Perfect Purity

Oil-Free Acne Wash

WITH 2% Salicylic Acid

Effective yet gentle cleanser for cleaner, clearer complexion

6 FL OZ (177 mL)